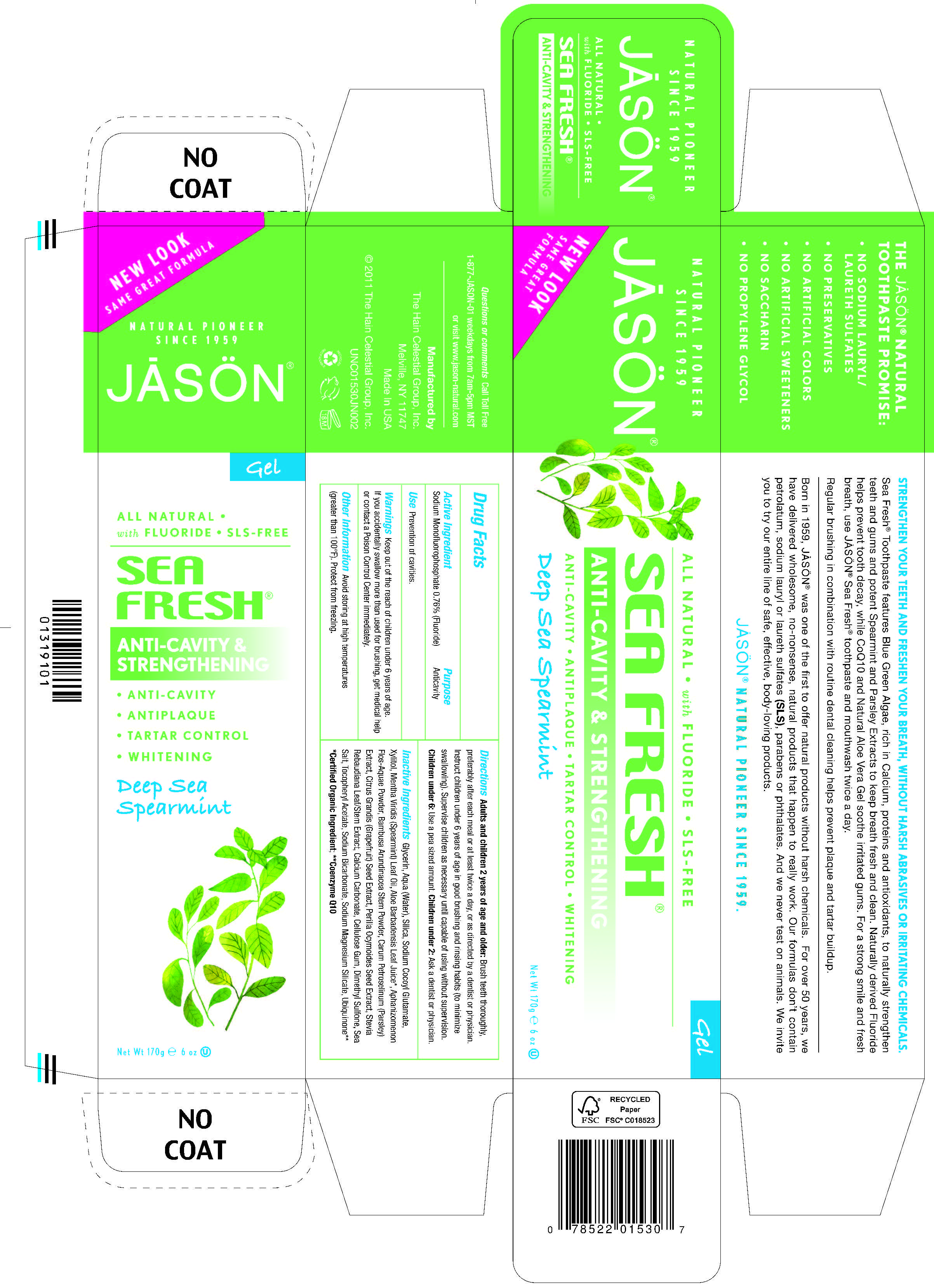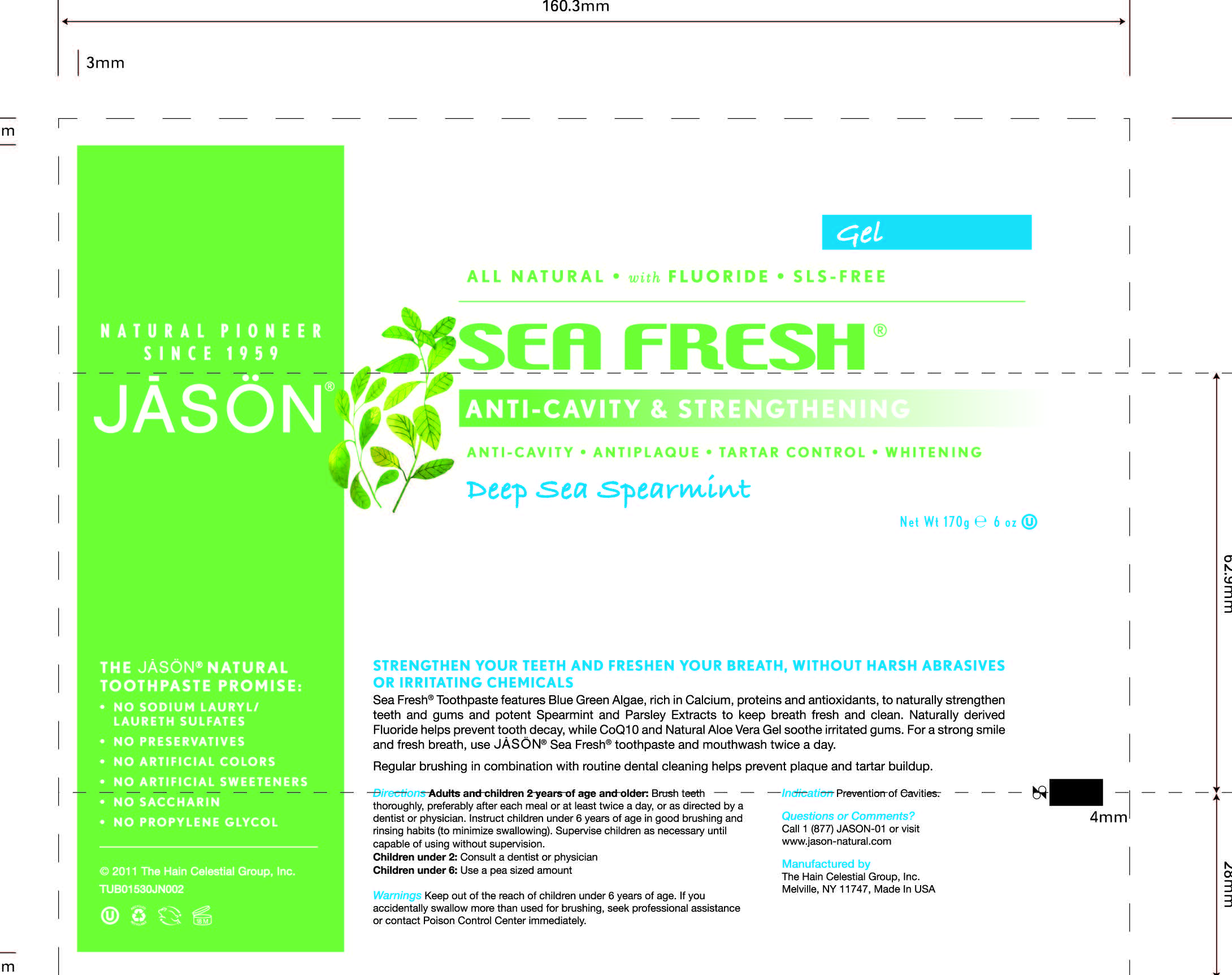 DRUG LABEL: Jason Sea Fresh Anticavity Strengthening Deep Sea Spearmint 
NDC: 61995-0104 | Form: GEL
Manufacturer: The Hain Celestial Group, Inc.
Category: otc | Type: HUMAN OTC DRUG LABEL
Date: 20120607

ACTIVE INGREDIENTS: SODIUM MONOFLUOROPHOSPHATE 0.76 g/100 g
INACTIVE INGREDIENTS: GLYCERIN; WATER; SILICON DIOXIDE ; SODIUM COCOYL GLUTAMATE ; XYLITOL; ALOE VERA LEAF; BAMBUSA ARUNDINACEA STEM ; CITRUS MAXIMA SEED; PARSLEY ; PERILLA FRUTESCENS SEED; STEVIA REBAUDIUNA LEAF; SPEARMINT OIL; APHANIZOMENON FLOS-AQUAE; UBIDECARENONE; MAGNESIUM SILICATE; SEA SALT; CALCIUM CARBONATE; CARBOXYMETHYLCELLULOSE SODIUM; DIMETHYL SULFONE; SODIUM BICARBONATE; .ALPHA.-TOCOPHEROL ACETATE

Drug Facts

ACTIVE INGREDIENT

Sodium Monofluorophosphate 0.76%

PURPOSE

Anticavity

INDICATIONS AND USAGE

Prevention of cavities

WARNINGS

Avoid storing at high temperatures (greater than 100°F). Protect from freezing.

Keep out of reach of children under 6 years of age.If you accidentally swallow more than used for brushing, get medical help or contact Poison Control Center immediately.

DOSAGE AND ADMINISTRATION

Adults and children 2 years of age or older: brush teeth throughly, preferably after each meal or at least twice a day, or as directed by a dentist or physician. Instruct children under 6 years of age in good brushing and rinsing habits (to monomize swallowing). Supervise children as necessary until capable of using without supervision. Children under 6: Use a pea sized amount. Children under 2: Ask a dentist or physician.

INACTIVE INGREDIENT

Glycerin, Aqua (Water), Silica, Sodium Cocoyl Glutamate, Xylitol, Mentha Viridis (Spearmint) Leaf Oil, Aloe Barbadensis Leaf Juice (1),Aphanizomenon Flos-Aquae Powder, Bambusa Arundinacea Stem Powder, Carum Petroselinum (Parsley) Extract,Citrus Grandis (Grapefruit) Seed Extract, Perilla Ocymoides Seed Extract, Stevia Rebaudiana Leaf/Steam Extract, Calcium Carbonate, Cellulose Gum, Dimethyl Sulfone, Sea Salt, Tocopheryl Acetate, Sodium Bicarbonate, Sodium Magnesium Silicate, Ubiquinone (2).

(1) Certified Organic Ingredients

(2) Coenzyme Q10

QUESTIONS

Questions? Call Toll Free 1-877-JASON-01 or visit www.jason-natural.com